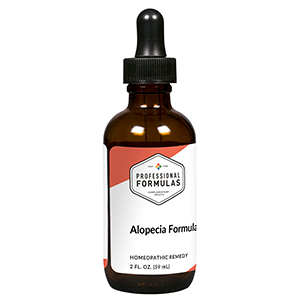 DRUG LABEL: Alopecia Formula
NDC: 63083-2139 | Form: LIQUID
Manufacturer: Professional Complementary Health Formulas
Category: homeopathic | Type: HUMAN OTC DRUG LABEL
Date: 20190815

ACTIVE INGREDIENTS: PHOSPHORUS 6 [hp_X]/59 mL; SULFUR 6 [hp_X]/59 mL; DAPHNE MEZEREUM BARK 9 [hp_X]/59 mL; SEPIA OFFICINALIS JUICE 9 [hp_X]/59 mL; ALUMINUM OXIDE 12 [hp_X]/59 mL; LYCOPODIUM CLAVATUM SPORE 12 [hp_X]/59 mL; ECLIPTA PROSTRATA WHOLE 12 [hp_X]/59 mL; GRAPHITE 12 [hp_X]/59 mL; THALLIUM 12 [hp_X]/59 mL
INACTIVE INGREDIENTS: ALCOHOL; WATER

C139

ACTIVE INGREDIENTS

Ustilago maydis 3X
Phosphorus 6X, 12X, 30X
Sulphur 6X, 12X, 30X
Mezereum 9X
Sepia 9X
Alumina 12X
Lycopodium clavatum 12X
Bhringraj 12X, 30X
Graphites 12X, 30X
Thallium metallicum 12X, 30X

QUESTIONS

Professional Formulas

PO Box 2034 Lake Oswego, OR 97035

INDICATIONS

Temporarily relieves the effects of unexplained hair loss.*

PURPOSE

*Claims based on traditional homeopathic practice, not accepted medical evidence. Not FDA evaluated.

WARNINGS

Consult a doctor if condition worsens or if symptoms persist. Keep out of the reach of children. In case of overdose, get medical help or contact a poison control center right away. If pregnant or breastfeeding, ask a healthcare professional before use.

Keep out of the reach of children.

PREGNANCY OR BREAST FEEDING

If pregnant or breastfeeding, ask a healthcare professional before use.

DIRECTIONS

Place drops under tongue 30 minutes before/after meals. Adults and children 12 years and over: Take 10 drops up to 3 times per day. Consult a physician for use in children under 12 years of age.

OTHER INFORMATION

Tamper resistant. If seal is broken, do not use. After opening, close container tightly and store at room temperature away from heat.

INACTIVE INGREDIENTS

20% ethanol, purified water.

LABEL

Est 1985

Professional Formulas

Complementary Health

Alopecia Formula

Homeopathic Remedy

2 FL. OZ. (59 mL)